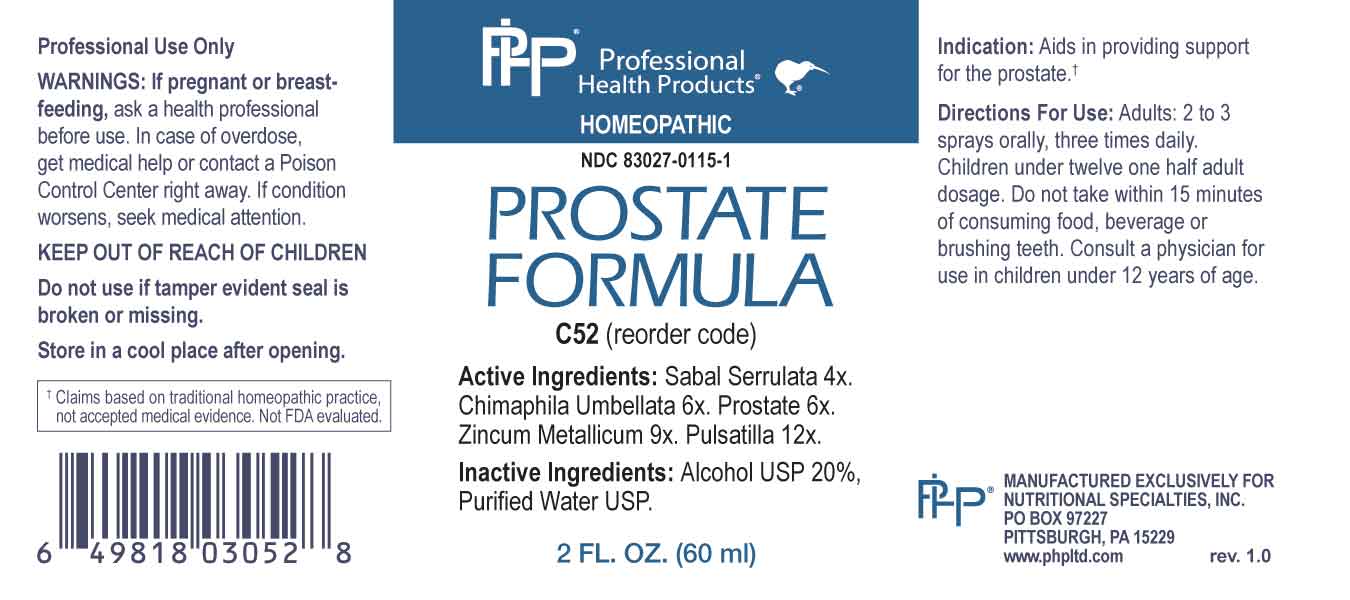 DRUG LABEL: Prostate Formula
NDC: 83027-0115 | Form: SPRAY
Manufacturer: Nutritional Specialties, Inc.
Category: homeopathic | Type: HUMAN OTC DRUG LABEL
Date: 20231006

ACTIVE INGREDIENTS: SAW PALMETTO 4 [hp_X]/1 mL; CHIMAPHILA UMBELLATA WHOLE 6 [hp_X]/1 mL; SUS SCROFA PROSTATE 6 [hp_X]/1 mL; ZINC 9 [hp_X]/1 mL; PULSATILLA PRATENSIS WHOLE 12 [hp_X]/1 mL
INACTIVE INGREDIENTS: WATER; ALCOHOL

DRUG FACTS:

ACTIVE INGREDIENTS:

Sabal Serrulata 4X, Chimaphila Umbellata 6X, Prostate 6X, Zincum Metallicum 9X, Pulsatilla 12X.

PURPOSE:

Aids in providing support for the prostate.†

†Claims based on traditional homeopathic practice, not accepted medical evidence. Not FDA evaluated.

WARNINGS:

Professional Use Only

If pregnant or breast-feeding, ask a health professional before use.

In case of overdose, get medical help or contact a Poison Control Center right away.

If condition worsens, seek medical attention.

KEEP OUT OF REACH OF CHILDREN

Do not use if tamper evident seal is broken or missing.

Store in a cool place after opening

KEEP OUT OF REACH OF CHILDREN:

In case of overdose, get medical help or contact a Poison Control Center right away.

DIRECTIONS:

Adults: 2 to 3 sprays orally, three times daily. Children under twelve one half adult dosage. Do not take within 15 minutes of consuming food, beverage or brushing teeth. Consult a physician for use in children under 12 years of age.

INDICATIONS

Aids in providing support for the prostate.†

†Claims based on traditional homeopathic practice, not accepted medical evidence. Not FDA evaluated.

INACTIVE INGREDIENTS:

Alcohol USP 20%, Purified Water USP.

QUESTIONS:

MANUFACTURED EXCLUSIVELY FOR

NUTRITIONAL SPECIALTIES, INC.

PO BOX 97227

PITTSBURG, PA 15229

www.phpltd.com

PACKAGE LABEL DISPLAY:

Professional

Health Products

HOMEOPATHIC

NDC 83027-0115-1

PROSTATE

FORMULA

2 FL. OZ (60 ml)